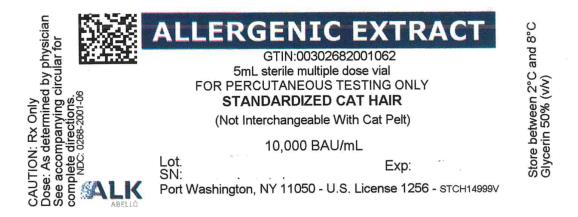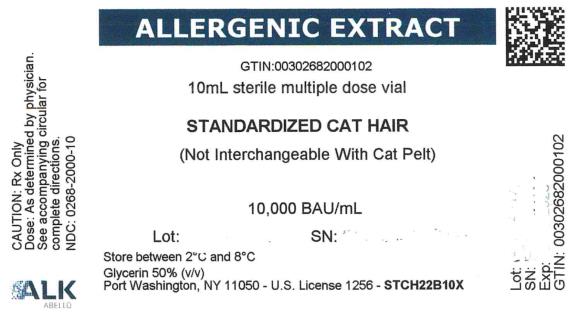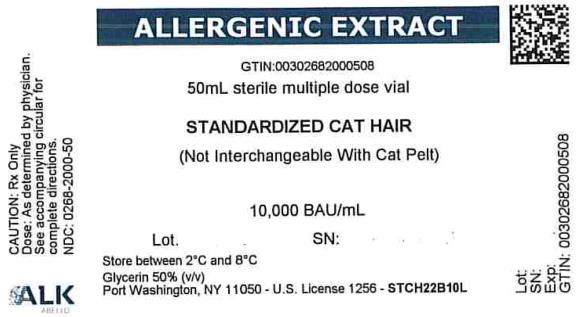 DRUG LABEL: Cat Hair, Standardized
NDC: 0268-2000 | Form: INJECTION, SOLUTION
Manufacturer: ALK-Abello, Inc.
Category: other | Type: STANDARDIZED ALLERGENIC
Date: 20200624

ACTIVE INGREDIENTS: FELIS CATUS HAIR 10000 [BAU]/1 mL
INACTIVE INGREDIENTS: SODIUM BICARBONATE 0.0025 g/1 mL; SODIUM CHLORIDE 0.005 g/1 mL; GLYCERIN 0.5 mL/1 mL; HYDROCHLORIC ACID; SODIUM HYDROXIDE

Standardized Cat Hair

ALK-Abelló, Inc.

Port Washington, NY

License 1256

ALLERGENIC EXTRACT

(STANDARDIZED CAT HAIR)

WARNING

This product should be used only by or under the direction of physicians experienced in administering allergens to the maximum tolerated dose and the emergency treatment of anaphylaxis, and only where adequate means for treating severe systemic reactions are immediately available.

This standardized cat hair extract is not interchangeable with non-standardized extracts, cat pelt extracts or with extracts labeled in allergy units per mL (AU/mL).

See Description, Warnings, and Dosage and Administration sections for further information.

Allergenic extracts may potentially elicit a severe life-threatening systemic reaction, rarely resulting in death^1. Because of the possibility of severe systemic reactions, the patient should be instructed in the recognition of anaphylactic symptoms, observed in the office for 20 to 30 minutes after each injection, and warned to return to the office if symptoms of an allergic reaction occur. Serious adverse events should be reported to the FDA MedWatch Program:

Adverse Event Reporting

5600 Fishers Lane Rockville, MD 20852-9787, (1 -800-FDA-1088)

Patients receiving beta-blockers may not be responsive to epinephrine or inhaled bronchodilators, and the risk of severely complicating the treatment of systemic reactions should be carefully considered before a decision to treat is reached. Care should also be taken with patients with unstable or steroid-dependent asthma, or with underlying cardiovascular disease.

Before administering this or any allergenic extract, physicians should be thoroughly familiar with the information in this insert, especially the Warnings, Precautions, and Adverse Reactions sections.

DESCRIPTION

Standardized cat hair extract is manufactured from source material obtained from the wash of cat hair clippings, which is then concentrated and absorbed onto powdered cat hair. Cat albumin and other serum-related non-Fel d 1 allergens, found in cat pelt extracts, have not been included in this extract. Cat albumin is not an important allergen for 80% of cat-sensitive patients^2. They are supplied as sterile solutions for scratch, intradermal or subcutaneous administration. The inactive ingredients are as shown in Table 1.

Table 1 Allergenic Extracts, Inactive Ingredients
Extract Formulation | Ingredient | Concentration (%)
Glycerinated | Sodium Chloride Sodium Bicarbonate Glycerin | 0.5 0.25 50 (v/v)

Standardized cat hair extracts containing 10 to19.9 Fel d 1 units per ml are assigned 10,000 Bioequivalent Allergy Units per ml (BAU/mI) based on quantitative skin testing^3. Standardized cat hair extracts containing 5 to 9.9 Fel d 1 units per ml are assigned 5,000 BAU/ml.

Isoelectric focusing (IEF) patterns of these standardized cat extracts have been shown to be predictive of the presence of non-Fel d 1 allergens. IEF has been adopted by the FDA as a release criterion. Therefore, all lots of Standardized Cat Hair extract are required to be compared by IEF to Center for Biologics Evaluation and Research (CBER) Cat Hair Extract Reference^4.

Allergenic extracts must be diluted before use in intradermal diagnosis or in the initial stages of treatment.

CLINICAL PHARMACOLOGY^5

The mode of action of allergenic extracts is under investigation.

The skin test reaction occurring in previously sensitized individuals is probably related to the interaction of antigen with IgE antibody and the subsequent release of histamine from mast cells. The therapeutic action of allergenic extracts may be related to the production of IgG (blocking) antibodies that remove allergenic proteins from the blood stream. Effective immunotherapy with allergenic extracts is usually associated with a shift in T-cell populations from a TH2 predominant type to a TH1 predominant population. This shift has been associated with changes in certain cytokines and other mediators. Immunotherapy also produces an initial rise in specific IgE levels, which then decrease as therapy continues.

Immunotherapy using cat extract has been studied by several investigators.

Generally, it is believed that hyposensitization with this product is helpful in reducing allergic symptoms associated with environmental exposure to cat allergens^6,7.

In skin test studies of ten patients who were determined to be allergic to cat, the average puncture test (using a bifurcated needle) to a Cat Hair Extract containing 10,000 BAU/ml produced a mean ∑ E of 82.4 mm with a range of 61 to 110 mm and a mean ∑ W of 15.6 mm with a range of 9 to 19 mm.

In this skin test study of cat-sensitive patients, the study subjects exhibited the following intradermal test responses:

 |  | BAU/ml to elicit 50 mm sum of diameter of erythema reaction.
Allergen | Number of Persons | Mean | Range
Cat Hair | 10 | 0.015 | 0.0007-0.21

INDICATIONS AND USAGE

Standardized Cat Hair allergenic extracts are indicated for the diagnostic skin testing and immunotherapy of patients whose histories indicate that they experience allergic symptoms upon natural exposure to the specific allergens.

CONTRAINDICATIONS

The product is contraindicated for use in subjects who are not clinically allergic to the specified allergen, or who are not reactive to ALK-Abelló extract. No other absolute contraindications to immunotherapy with allergenic extracts are known.

However, the risk of serious systemic anaphylactic reactions to any potent allergenic extract suggests a number of preexisting conditions that should be considered relative contraindications. Among those conditions are acute infections, immune disease, severe cardiac disease pulmonary diseases such as asthma with a significant irreversible component, and treatment with β-adrenergic antagonist drugs (''beta-blockers''). See also Warnings, Precautions, and Adverse Reactions.

WARNINGS

See additional warnings given in the box at the beginning of this insert.

Do not use this extract or allow its use until you have read this insert, and have taken adequate precautions to prevent inadvertent dosage errors. See Dosage and Administration for further information.

Some patients are highly sensitive to allergenic extracts, and in such patients even a small skin test dose could result in a serious systemic reaction. Adequate means to treat such reactions must be immediately available, including the following equipment^8: stethoscope and sphygmomanometer; tourniquets, syringes, hypodermic needles, and large-bore (14 gauge) needles; aqueous epinephrine HCI 1:1000;oxygen, intravenous fluids and the equipment for administering them; oral airway; diphenhydramine or similar antihistamine; aminophylline and corticosteroids for intravenous injection; and vasopressor.

Observing the following precautions will reduce the risk of serious systemic reactions:

- Do not begin immunotherapy without establishing the appropriate initial dose by skin testing (see Dosage and Administration), and do not inject the undiluted extract concentrate at any time unless tolerance has been demonstrated.
- When changing to an extract from a different manufacturer establish the proper dosage by skin testing.
- When changing to a different lot of extract, reduce the dose by 50-75%; this is particularly important after using an extract that is near its expiration date.
- Take care to properly prepare, label store and control all dilutions.
- Use caution in dosing of high-risk steroid-dependent labile asthmatics.

DO NOT GIVE INTRAVENOUSLY. After inserting the needle subcutaneously, but before injecting the dose, retract the plunger of the syringe slightly. If blood appears in the syringe, discard the syringe and its contents and repeat the injection at another site. Subcutaneous injection is recommended because intracutaneous or intramuscular injections are more likely to produce local reactions.

Observe the patient at 20 to 30 minutes after injection, and be alert for the signs of impending reaction. Make sure the patient understands that serious delayed reactions can occur later on, how to recognize them, and what to do if they occur.

Patients who are receiving beta-blocking medication are high-risk patients for immunotherapy, because systemic reactions to the extract may be more severe in such patients^9, and because the beta-blocker may impair the ability to reverse the reaction^10 in such patients. This risk should be carefully weighed before a decision to treat is reached. Care should also be taken with patients with unstable or steroid-dependent asthma or with underlying cardiovascular disease.

This and any allergenic extract should be temporarily withheld or its dosage reduced under any of these conditions^11:

- When the patient has an unexpectedly severe local or any systemic reaction to the previous dose.
- If the patient is experiencing allergic symptoms such as rhinitis or asthma or is ill with flu or infection accompanied by fever.
- If an unusually long time has passed since the previous injection.
- If the patient is exposed to excessive amounts of clinically relevant allergen prior to therapy.

Allergic patients differ widely in their sensitivity to this or any allergenic extract, and no single dosage regimen can be recommended for all patients. Progression to the next higher dose requires tolerance of the previous one, and the regimen must be modified if any of the conditions described above occur. Such modifications should include weaker dilutions and smaller dosage increments.

PRECAUTIONS

General:

Patient compliance is an important consideration in the decision to initiate immunotherapy with any potent allergenic extract. Therapy should not be initiated if in the judgment of the physician the patient cannot be depended upon to respond promptly and properly to an impending adverse reaction, or to report such reactions.

Care must be taken to control the preparation, labeling, storage, and use of dilutions.

The ramifications of inadvertent overdosage are severe (see Warnings and Adverse Reactions), and so procedural safeguards such as training programs, color-coded labeling, storage controls, and auditing are recommended.

As with the administration of any parental drug, observe all aspects of aseptic technique. In both testing and treatment, use a separate sterilized needle and syringe for each individual patient, to prevent transmission of hepatitis and other infectious agents from one person to another.

Information For Patients:

The patient should be told to remain in the office for 20 to 30 minutes after injection, and be alert for the signs of impending reaction.

The patient should be instructed that serious delayed reactions can occur later on and that these must be reported to the physician immediately. These reactions include swelling or tenderness at the site of injection, rhinorrhea sneezing, coughing, shortness of breath nausea dizziness wheezing, rash or faintness.

Drug Interaction:

Patients who are receiving beta-blocking medication are high-risk patients for immunotherapy, because systemic reactions to the extract may be more severe in such patients^9, and because the beta-blocker may impair the ability to reverse the reaction^10.

The patient should not take antihistamines prior to skin testing, since the pharmacological actions of such drugs might interfere with the skin test response.

Discontinue regular antihistamines for 3-10 days and contacting antihistamines such as Astemizole for as long as 60 days before skin testing^12. Also, be aware that the concurrent use of antihistamines during immunotherapy might mask an otherwise observable local reaction to an injection.

Carcinogenesis, Mutagenesis, Impairment Of Fertility:

No long term studies with this or any allergenic extract have been carried out to determine their effect on carcinogenesis, mutagenesis, or impairment of fertility.

Pregnancy Category C:

Animal reproduction studies have not been conducted with allergenic extracts. It is also not known whether allergenic extracts can cause fetal harm when administered to a pregnant woman or can affect reproductive capacity. Allergenic extracts should be given to a pregnant woman only if clearly needed.

On the basis of histamine's known ability to contract uterine muscle any reaction that would release significant amounts of histamine whether occurring from allergen exposure or immunotherapy overdose, should be avoided.

Nursing mothers:

It is not known whether this drug is excreted in human milk.

Because many drugs are excreted in human milk, caution should be exercised when allergenic extracts are administered to a nursing woman.

Geriatric Use:

Clinical studies of allergenic extracts have not included sufficient numbers of patients aged 65 and over to determine whether they respond differently from younger patients. Other reported clinical experience has not identified differences in responses between the elderly and younger patients. In general, dose selection for an elderly patient should be cautious, usually starting at the low end of the dosing range, reflecting the greater frequency of decreased hepatic, renal or cardiac function, and of concomitant disease or other drug therapy.

Pediatric Use:

Clinical studies of allergenic extracts did not include sufficient numbers of pediatric patients to determine whether they respond differently from older patients. Other reported clinical experience has not identified differences in responses between pediatric and adult patients. In general, dose selection for a pediatric patient should be cautious, usually starting at the low end of the dosing range.

ADVERSE REACTIONS

Severe anaphvlactic reactions to this extract can occur in extremely allergic patients and at any dosage level. Do not use this extract unless you are prepared to deal with these reactions, and until you have read and understood the warnings, precautions, and dosage and administration sections of this insert.

The most serious systemic reaction that can occur is anaphylactic shock which while rare, is life threatening and must be treated immediately. Among other systemic reactions that have occurred are laryngeal edema, fainting, pallor bradycardia, hypotension, bronchospasm, angioedema, cough, sneezing, conjunctivitis, rhinitis, and urticaria.

Should a serious systemic reaction occur:

- Inject 0.3-0.5 ml of 1:1000 epinephrine into the opposite arm; this may be repeated every 5 to 10 minutes, as a succession of smaller doses is more effective and less dangerous than a single larger one. Use a smaller dose for infants and children, in the range of 0.01 ml/kg of body weight.
- Apply a tourniquet proximal to the injection site; loosen it at least every 10 minutes interval.
- Inject no more than 0.1 ml of 1:1000 epinephrine at the injection site, to delay the absorption of the remaining extract.
- Beta adrenergic agonists or aminophylline may be helpful in alleviating bronchospasm and airway obstruction. Other treatments that may be of benefit include H1 antihistamines (e.g., 1 mg/kg diphenhydramine) and glococorticoids (e.g., 120 mg methylprednisolone).

These measures will almost always reverse the reaction but in the rare instances when they do not, then the full armamentarium of emergency medicine may be required, among them: direct laryngoscopy direct current cardioversion, tracheotomy, and intracardiac injection of drugs^8.

The occurrence of a severe systemic reaction to an injection of this extract does not contraindicate further therapy, but the next dose given should be reduced by at least 90% and raised very slowly thereafter. If a pattern of systemic reactions- even very mild ones- appears, then the benefits of continued treatment must be carefully weighed against the substantial demonstrated risk.

Local reactions, even relatively severe but transient redness, swelling and discomfort, are the normal physiologic response to the allergens and to the volume of the fluid injected, and in their milder forms are not unexpected. Local reactions generally subside quickly and do not require treatment, but application of cold to the injection site or other symptomatic measures may be useful. However, severe local reactions should be considered a warning of potential systemic reaction if that dosage is continued. Always reduce the dose substantially if such a local reaction occurs.

Overdosage:

See Adverse Reactions section.

DOSAGE AND ADMINISTRATION

Dilution

Allergenic extract concentrates must be diluted before use in intradermal skin testing or the initial stages of immunotherapy. As with any parenteral product, always use careful aseptic technique in preparing dilutions, assuring that the vials, diluents, and syringes are sterile, and that the dilutions are prepared under aseptic conditions, Sterile diluents that can be used include Normal Saline, Buffered Saline, 50% glycerin or Albumin Saline (HSA).

To obtain the concentrations required for intradermal testing or for the initial stages of immunotherapy, prepare serial 5 or 10 fold dilutions of the concentrate, to achieve the concentrations specified in Table 2 or 3, below. The relatively small 0.5 ml volume conserves the original concentrate, and is convenient because sterile diluent is readily available in prefilled 2.0 and 4.5 ml volumes.

Table 2 Examples of Ten-fold Dilution Series
Dilution Number | Add This Volume/Dilution of Extract | To this Diluent Volume | To Obtain Extract at the Following Concentration (BAU/ml)
0 1 2 3 4 5 6 | Concentrate 0.5 ml concentrate 0.5 ml dilution #1 0.5 ml dilution #2 0.5 ml dilution #3 0.5 ml dilution #4 0.5 ml dilution #5 | __ 4.5 ml 4.5 ml 4.5 ml 4.5 ml 4.5 ml 4.5 ml | 10,000 1,000 100 10 1.0 0.10 0.01

Table 3 Examples of Five-fold Dilution Series
Dilution Number | Add This Volume/Dilution of Extract | To this Diluent Volume | To Obtain Extract at the Following Concentration (BAU/ml)
0 1 2 3 4 5 6 | Concentrate 0.5 ml concentrate 0.5 ml dilution #1 0.5 ml dilution #2 0.5 ml dilution #3 0.5 ml dilution #4 0.5 ml dilution #5 | __ 2.0 ml 2.0 ml 2.0 ml 2.0 ml 2.0 ml 2.0 ml | 5,000 1,000 200 40 8 1.6 0.32

For each vial, record the date of dilution on the label.

Skin Testing

Scratch or prick-puncture testing should be performed using the 10,000 BAU/ml concentrate, a negative control (diluent) and a positive control (histamine 1.8 mg/ml). Extract for intradermal testing can be prepared by diluting the concentrate with any appropriate aqueous sterile diluent, as described above. A 100 BAU/ml concentration is also available for intradermal testing.

The following skin testing protocol can be recommended:

1. The location for both prick and intradermal testing is usually the flexor surface of the forearm. Use aseptic technique throughout.
2. Perform a preliminary skin prick test with the extract concentrate, by placing a drop of the extract on the skin and then using a needle to prick the skin gently through the drop. Use a normal diluent as negative control and histamine as a positive control. Read the test after 15 minutes. Patients reacting strongly to the prick test should be considered highly sensitive to the extract, and suitable precautions should be taken. A suggested grading system appears in Table 4. If the histamine control is negative, the possibility of skin non-reactivity must be considered.
3. Begin intradermal testing, generally starting at the 100 BAU/ml dilution if the prick test was negative, or at 0.1 or 0.01 BAU/ml if the test was positive or if no prick test was done. Use a separate, sterilized syringe and needle for each extract and each patient. Introduce the needle into the superficial skin layers until the bevel is completely buried, then slowly inject approximately 0.02 - 0.05 ml.
4. Measure the wheal and erythema after 15 minutes, and determine the degree of response to the injection, in comparison to the negative control. A suggested grading system appears in Table 5.
5. If the intradermal reaction is negative at the initial concentration, continue intradermal testing with 10-fold increments in the concentration until a clearly positive response has been obtained or a peak concentration of 100 BAU/ml has been tested, whichever occurs first.

Table 4 Skin Test Grading System^12
Grade | Wheal Results
0 + ++ +++ ++++ | No Wheal/same size as negative <Half the Histamine Diameter Half the Histamine Diameter Same Size as Histamine Control Size of Histamine Control +2mm

Table 5 Intradermal Skin Test Grading System^13
 | Mean Diameters (mm)
Grade | Wheal | Erythema
0 ± 1+ 2+ 3+ 4+ | <5.0 5.0-10.0 5.0-10.0 5.0-10.0 5.0-10.0 or pseudopods >15.0, many pseudopods | <5.0 5.0-10.0 11.0-20.0 21.0-30.0 31.0-40.0 >40.0

The interpretation of the skin response is based on the size of the wheal, the size of the erythema, and the appearance of irregular, spreading, pseudopodllike projections from the test area. The presence of the latter indicates marked hypersensitivity. A patient is considered sensitive to the test extract if there is a reaction of 1 + or greater at a concentration of 100 BAU/ml or less, providing that the 1 + reaction is in relation to the negative control.

Immunotherapy

Administer the extract solution subcutaneously, using a suitable sterile 1 ml syringe and a 25-27 gauge 1/4 to 5/8 inch needle. The injections are typically given in the lateral aspect of the upper arm.

Dosage of allergenic extracts is a highly individualized matter^1^2, and varies according to the degree of sensitivity of the patient, the clinical response, and tolerance of the extract administered previously.

A safe starting dose for any allergic patient is that dose which on intradermal testing produces a 1 + reaction. For most patients a starting dose that is 0.1 ml of 0.01 BAU/ml dilution of the extract concentrate should be well tolerated, although in some very sensitive patients a more dilute concentration may be required.

If no untoward symptoms are observed following the initial injection, the dose can be increased gradually for each subsequent injection until the injection volume reaches 0.6 -0.8 ml. Then begin using the next more concentrated ten-fold dilution, and proceed with this dosage pattern until the maintenance dose-defined as that dose that either relieves the patient's symptoms or is the highest that the patient can tolerate is reached. Care must be taken, however, in administering a volume greater than 0.2 ml of any extract in 50% glycerin; such injections can be painful to the patient due to the glycerin content.

After each injection, evaluate the patient's skin reaction and overall response to determine whether the next scheduled dose can be given:

- If a single dose results in more than a moderate local reaction (>50 mm wheal) within 1/2 hour, the same dose should be repeated at the next visit - or visits - until the patient has tolerated it.
- lf any systemic manifestation of sensitivity occurs during or following a visit, or if a single dose results in an excessive local reaction (> 100 mm wheal) within ½ hour, the total dosage for the next visit should be reduced to half of the dose that caused the reaction.
- Delayed local reactions (occurring 24-48 hours after injection) are relatively common, and do not appear to predict difficulties with future doses. As a rule, therefore, dosage adjustment is not required in most instances. However, at the physician's discretion and for the comfort of the patient, if delayed large local reactions over 10 mm are reported, the subsequent dose should be held at the same level as the one causing the reaction.

The optimal interval between doses of allergenic extract has not been definitely established. However, as is customarily practiced, injections are given 1, 2, or 3 times per week until the maintenance dose of extract is reached. At this time, the injection interval may be increased to 2 weeks, then to 3 weeks and finally to 4 weeks depending on the clinical status. lf the patient does not return for 6 to 8 weeks after the last injection, the dose should be reduced to 25% of the last dose.

If longer than 8 weeks, a dose reduction of one, two or three dilutions may be made depending on a consideration of the components and the patient’s sensitivity. The dosage and the interval between injections may need to be modified according to the clinical response of the patient. When switching patients to fresh extract, the initial dose should be reduced to one-quarter of the previous dose.

Duration of treatment: Careful selection of allergens and cautious progression to maximally tolerated doses are important elements in the success of immunotherapy. The optimal length of treatment with allergen immunotherapy is unknown. A treatment period of 3 to 5 years is common, although continuation for longer periods may be appropriate^1^3.

Allergenic extracts, as any parenteral drug product should be inspected visually for evidence of foreign material or discoloration prior to administration. Some variation in color is normal and a minor level of extract precipitate may occur with some extracts, but do not use the extract if there is any question of its condition exists.

HOW SUPPLIED

These allergenic extract concentrates are supplied as sterile solutions in rubber stoppered glass vials. The concentrate is available in 5, 10, 30 and 50 ml size serum vials for Immunotherapy at 5,000 BAU/ml and 10,000 BAU/mI; intradermal dilution is available in 5 ml vial size at a concentration of 100 BAU/ml; and the scratch test products are available in 5 ml dropper vials at a concentration of 10,000 BAU/ml.

To ensure maximum potency for the entire dating period, extract concentrates contain 50% glycerin (v/v) unless otherwise instructed by the physician.

Diluted extracts, special mixtures and prescription treatment sets are available at tile request of the physician.

Storage: The extract concentrate and all dilutions should be kept refrigerated at 2-8ºC. Do not freeze, and do not use the extract concentrate after the expiration date printed on the vial label. Extracts that contain less than 50% v/v glycerin are less stable,

LIMITED WARRANTY

We warrant that this product was prepared and tested according to the applicable standards of the FDA and was true to label when it left our hands. Because of biological differences in individuals, because this product is manufactured to be potent, and because we have no control over the conditions of use, we cannot and do not warrant either a good effect, or against an ill effect following its use. This label sets forth the complete and excluding statement of all the terms of any warranty, express or implied (including the warranty of merchantability) between ALK-Abelló, Inc., the prescriber, and the user of this product. Such representations and warranties shall not be varied, supplemented, qualified or interpreted by any prior course of dealing between the parties, or by any usage of trade unless specifically authorized in writing, signed by any officer of the corporation.

ALK-AbeIló, Inc.

US License 1256

800-252-9778

In TX: 512-251-0037

Revised October 2008 731B

REFERENCES

1. Reid, M.J., et aI.:2 Survey of fatalities from Skin testing and immunotherapy 1985-1989. J. Allergy Clin. Immunnol. 92:6-15, 1993.
2. Ohman, J.L., Marsh, D.G., Goldman, M.: Antibody response following immunotherapy with cat pelt extract. J Allergy Clin. Immunol, 69:320-326, 1982, .
3. Turkeltaub, P.C., Rastogi, S.C., Baer, H.: OBRR skin test method for evaluation of subject sensitivity to standardized allergenic extracts and for assignment of allergy units to reference preparations using ID5OEAL method.
4. Methods Manual, Laboratory of Allergenic Products, Food and Drug Administration, October 1 993.
5. Van Metre, T.E., and Adklnson, N.F. in: Allergy Principles and Practice, Fourth Edition, 1489-1509, 1993. C.V, Moseby Co.
6. Lilja, G., Sundin, B,, Graff-Lonnevig, V., Heidlin, G., Heilborn, H., Norrlind, K., Pegelow, K-O., Lowenstein, H.: Immunotherapy with cat and dog dander extracts, IV. Effects of 2 years of treatment. J Allergy Clin. Immunol. 83:37-44,1 1989.
7. Alvarez-Cuesta, E,, Cuesta, J., Puyana, J., Cureta, C., Bianco, A.: Clinical effectiveness of immunotherapy with cat extract (Abstract). J Allergy Clin. lmmunol. 87:198, 1991.
8. Anderson, J,A,, et, aI.: Personnel And Equipment To Treat Systemic Reactions Caused By Immunotherapy With Allergenic extracts. J. Allergy Clin Immunol 77(2):271 -273, 1986.
9. Jacobs, R.L. et. Al.: Potentiated Anaphylaxis In Patients with Drug Induced Beta Adrenergic Blockade. J. Allergy Clin Immunol 68: 125, 1981.
10. Bickell, W.H., and Dice, W.H.: Military Antishock Trousers ln A Patient With Adrenergic Resistant Anaphylaxis. Ann Emerg Med. 13:189, 1984.
11. Norman, P.S., and Van Metre, T.E.: The Safety of Allergenic Immunotherapy. J. Allergy Clin lmmunol.85: 522, 1990.
12. Middleton, E,, et aI: Allergy: Principles and Practice C.V. Mosely Co. 1993.
13. Spector, S. L. and Nicklas, R. A.: ''Practice Parameters for Diagnosis and Treatment of Asthma,''J, Allergy Clin lmmunol, 96:(5): 810, 1995.

PRINCIPAL DISPLAY PANEL

ALLERGENIC EXTRACT
GTIN:
5mL sterile multiple dose vial
STANDARDIZED CAT HAIR
10,000 BAU/mL

PRINCIPAL DISPLAY PANEL

ALLERGENIC EXTRACT
GTIN:
10mL sterile multiple dose vial
STANDARDIZED CAT HAIR
10,000 BAU/mL

PRINCIPAL DISPLAY PANEL

ALLERGENIC EXTRACT
GTIN:
50mL sterile multiple dose vial
STANDARDIZED CAT HAIR
10,000 BAU/mL